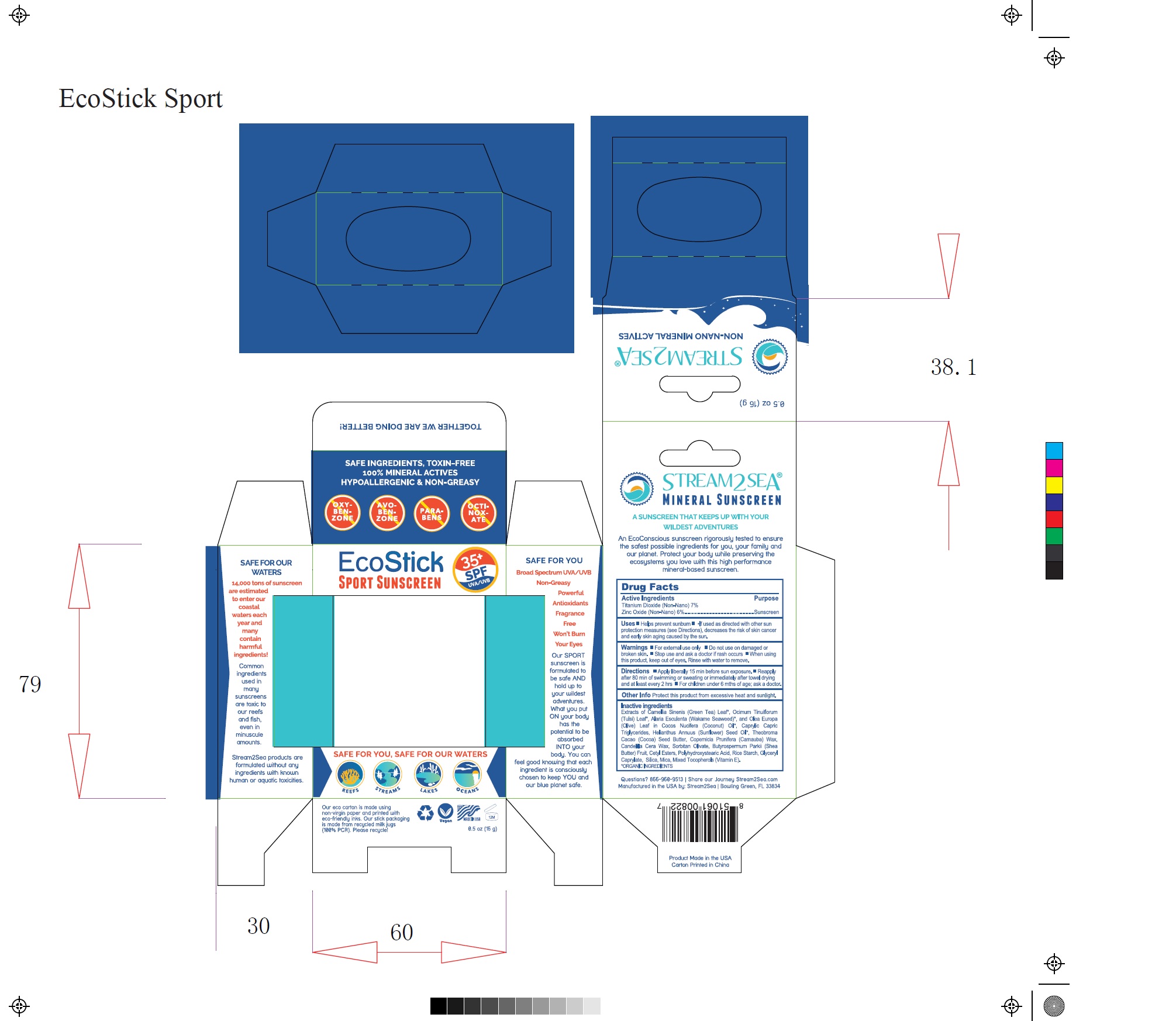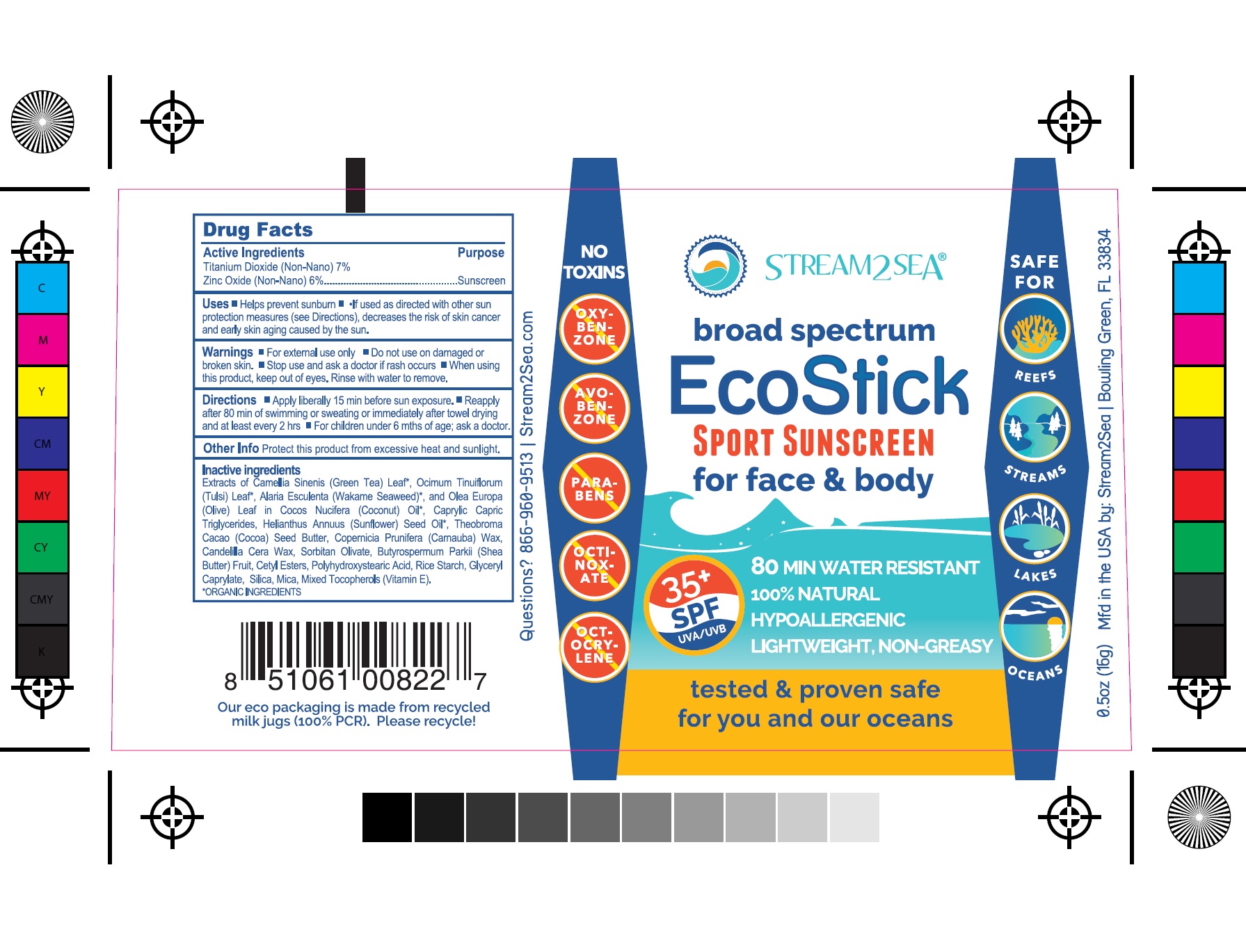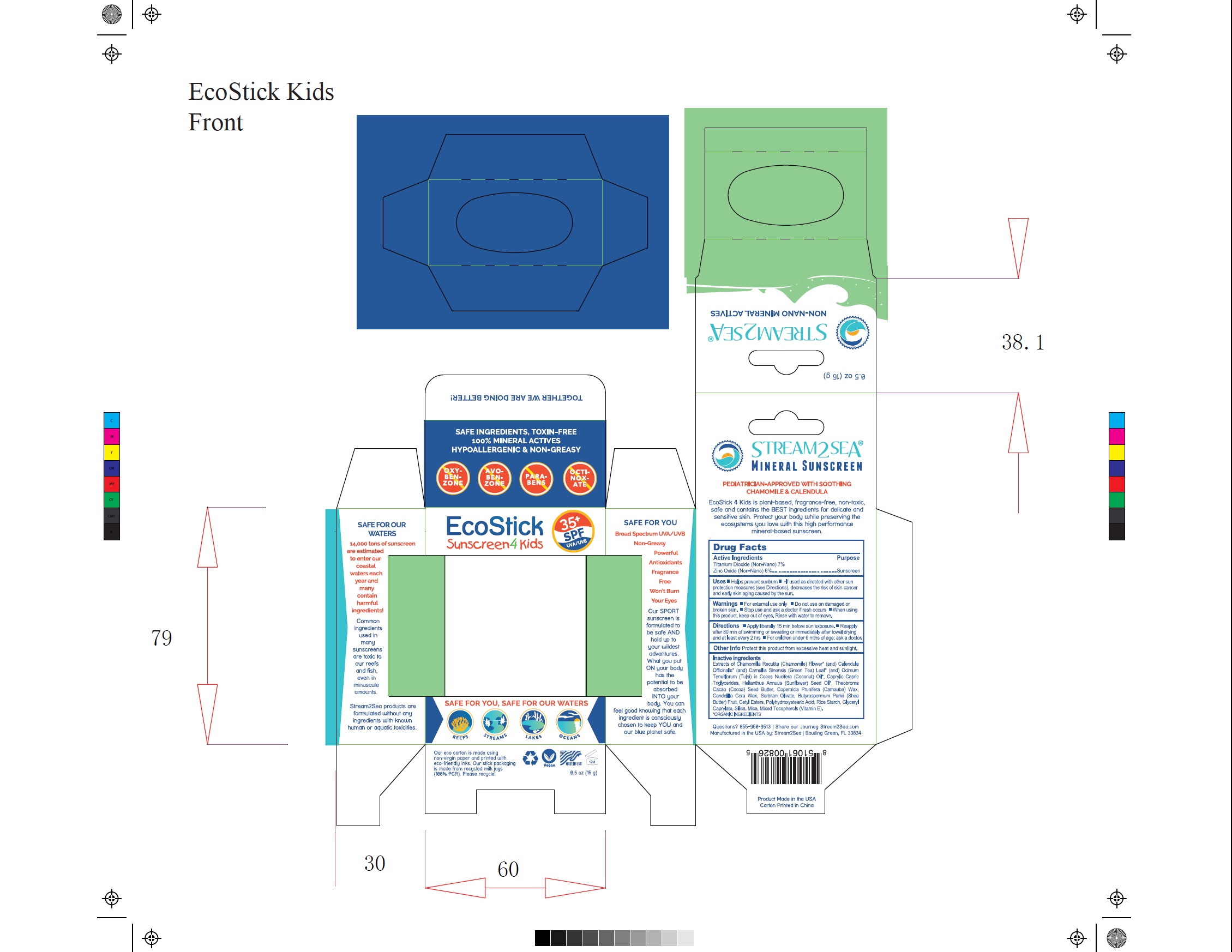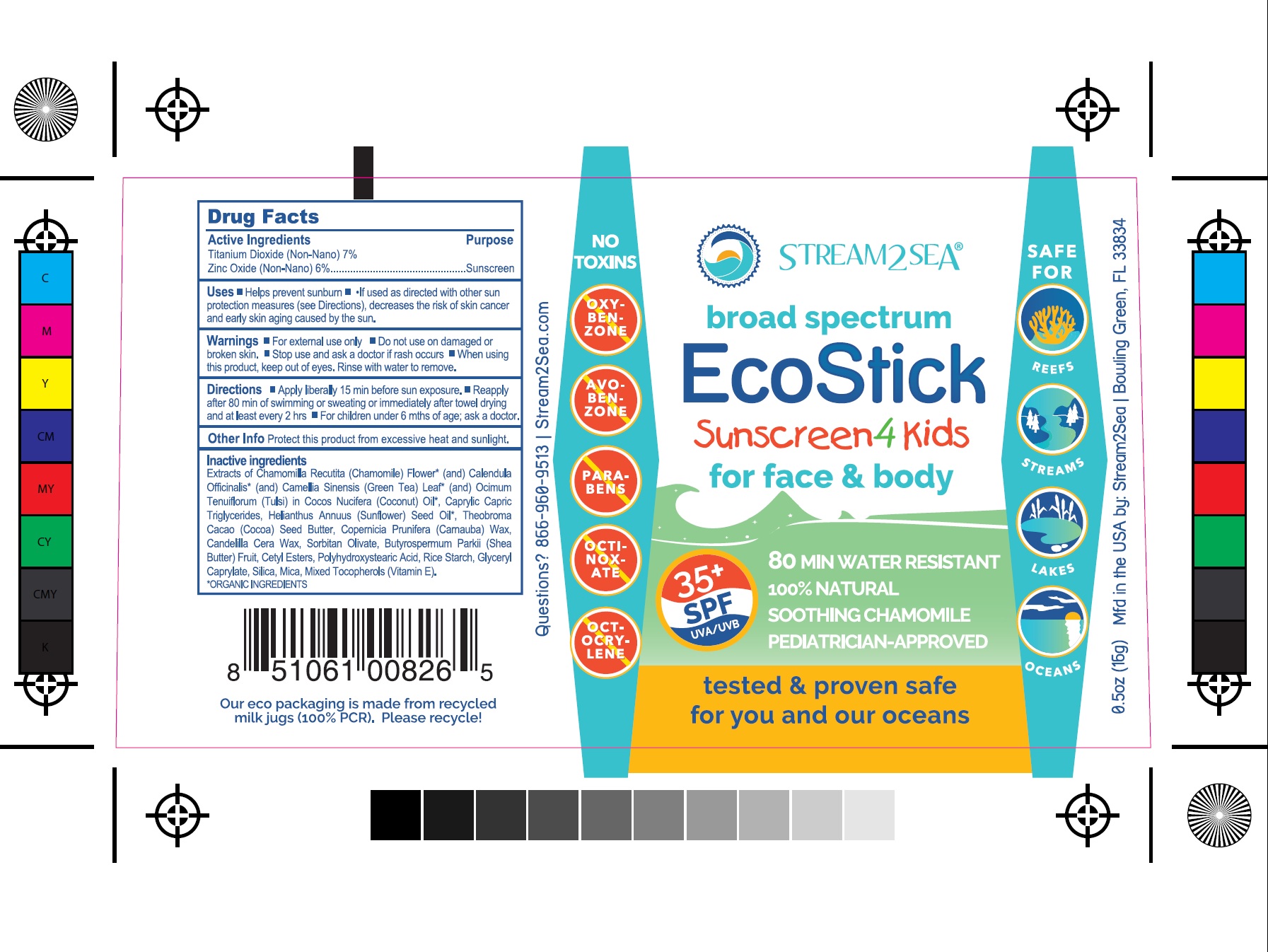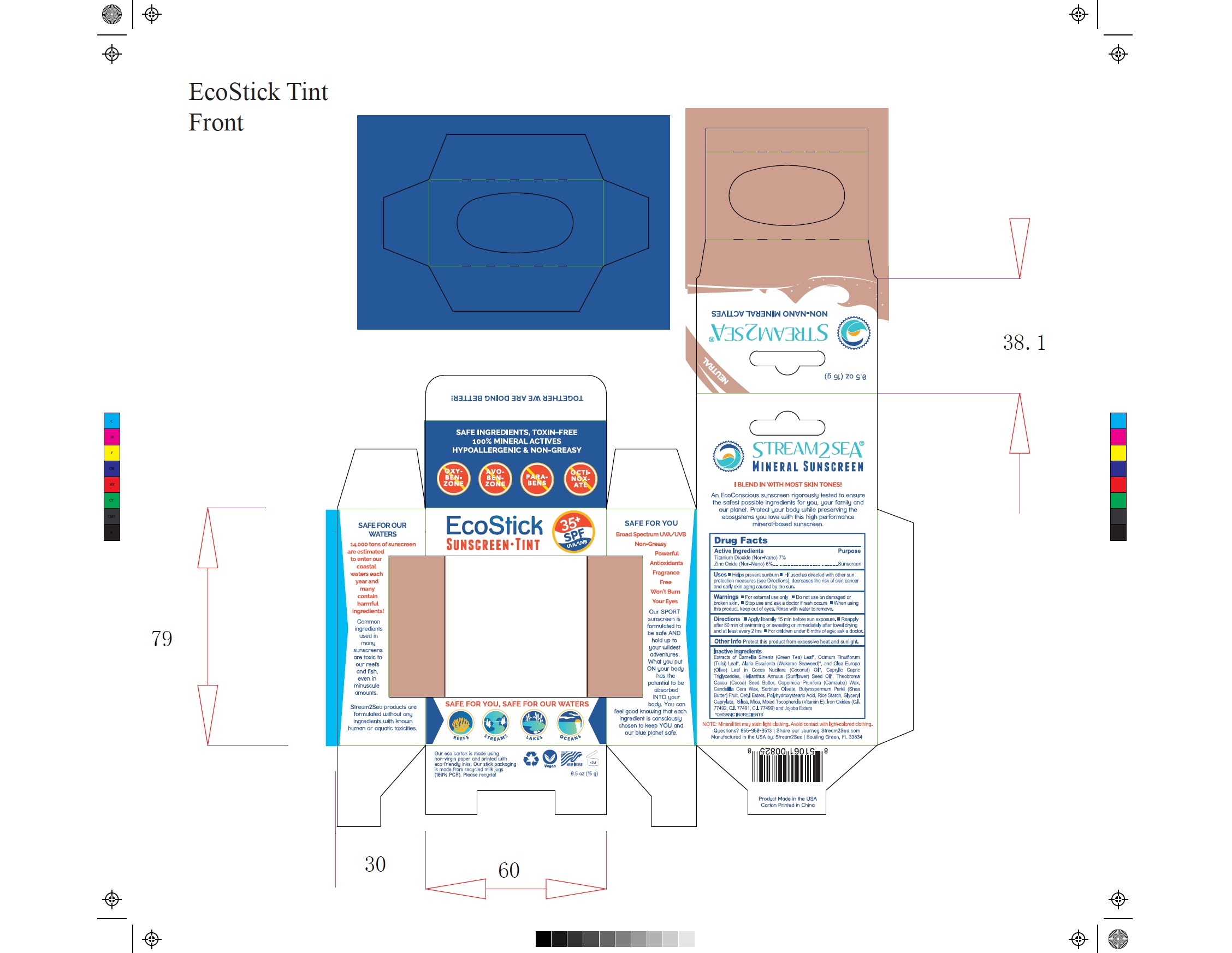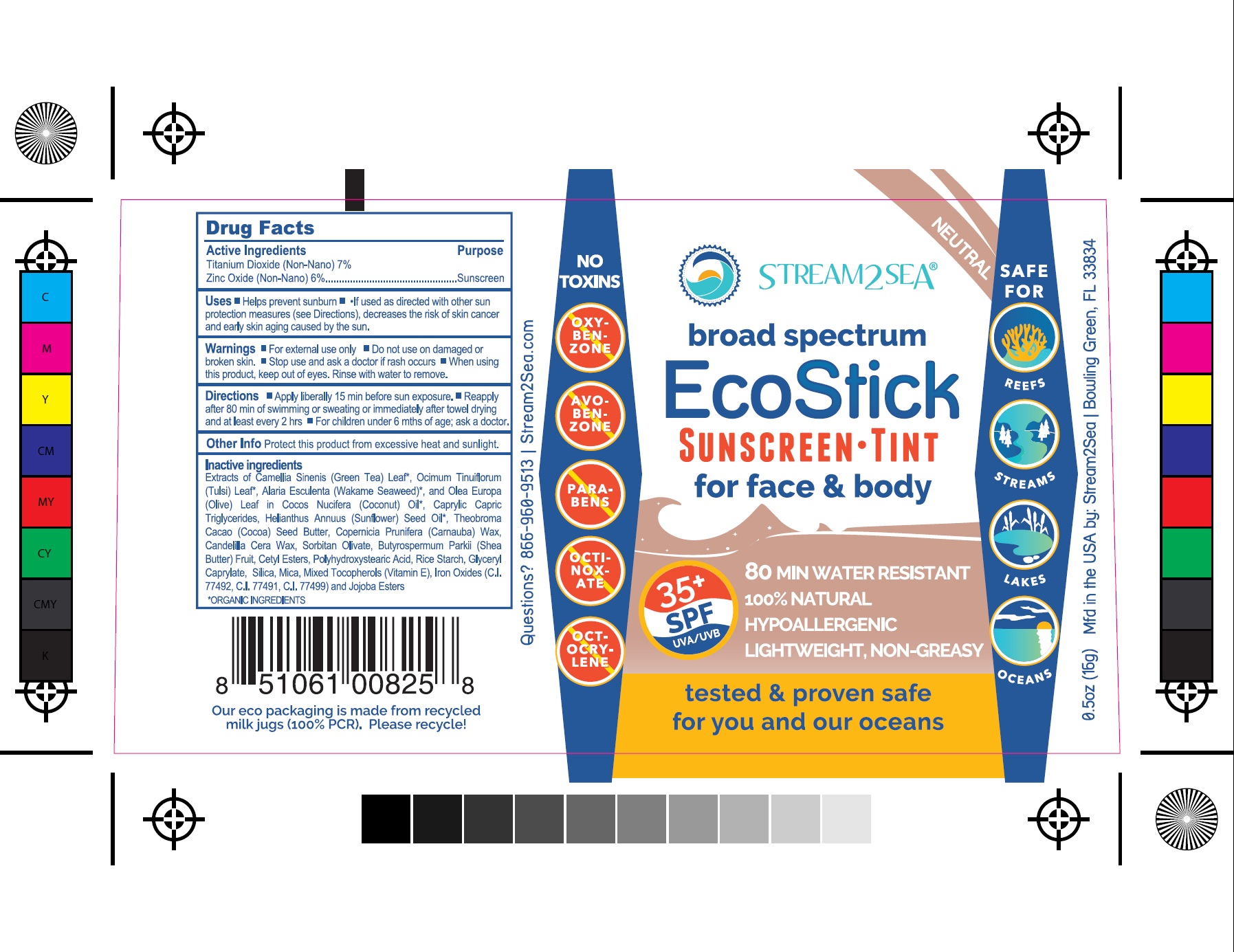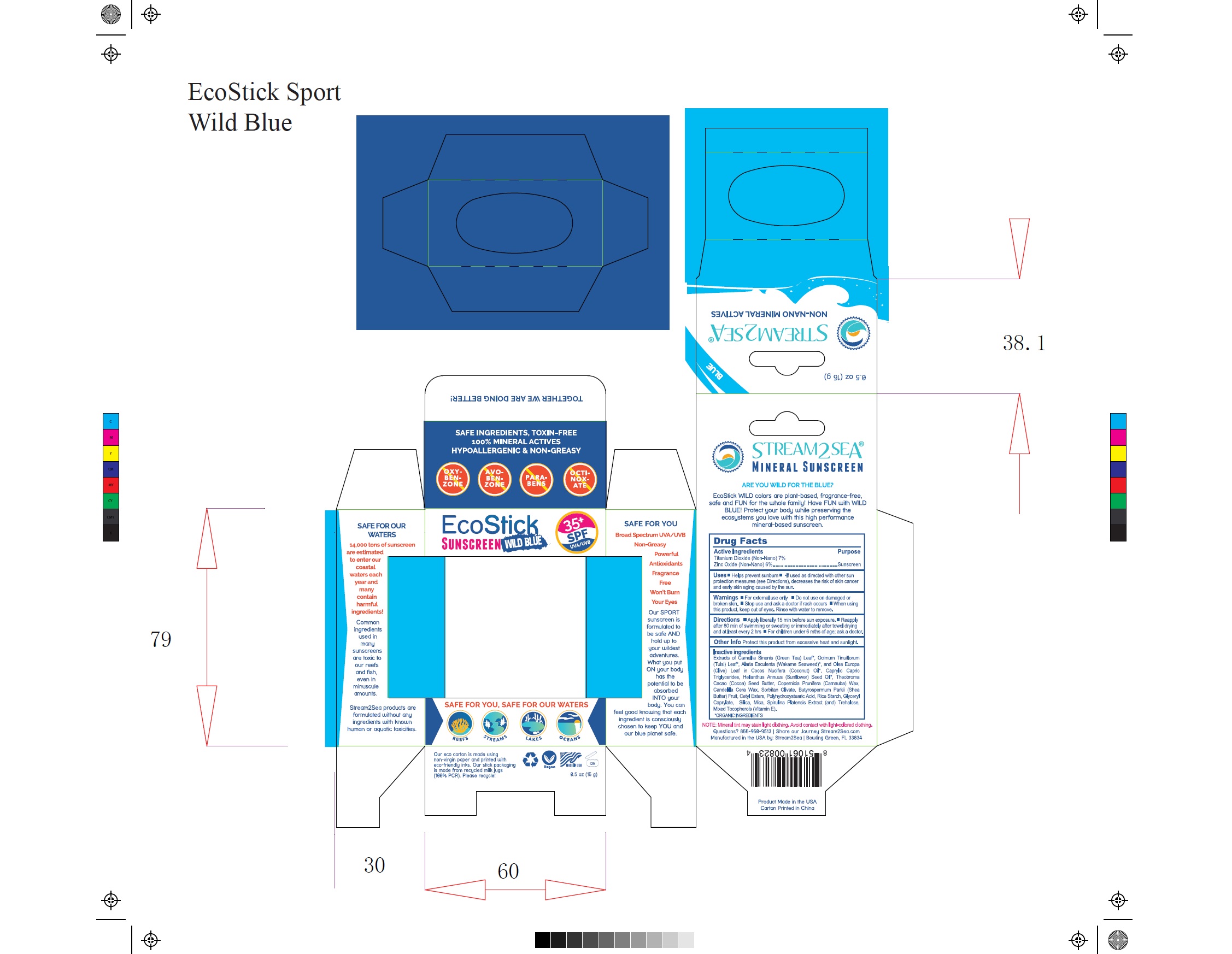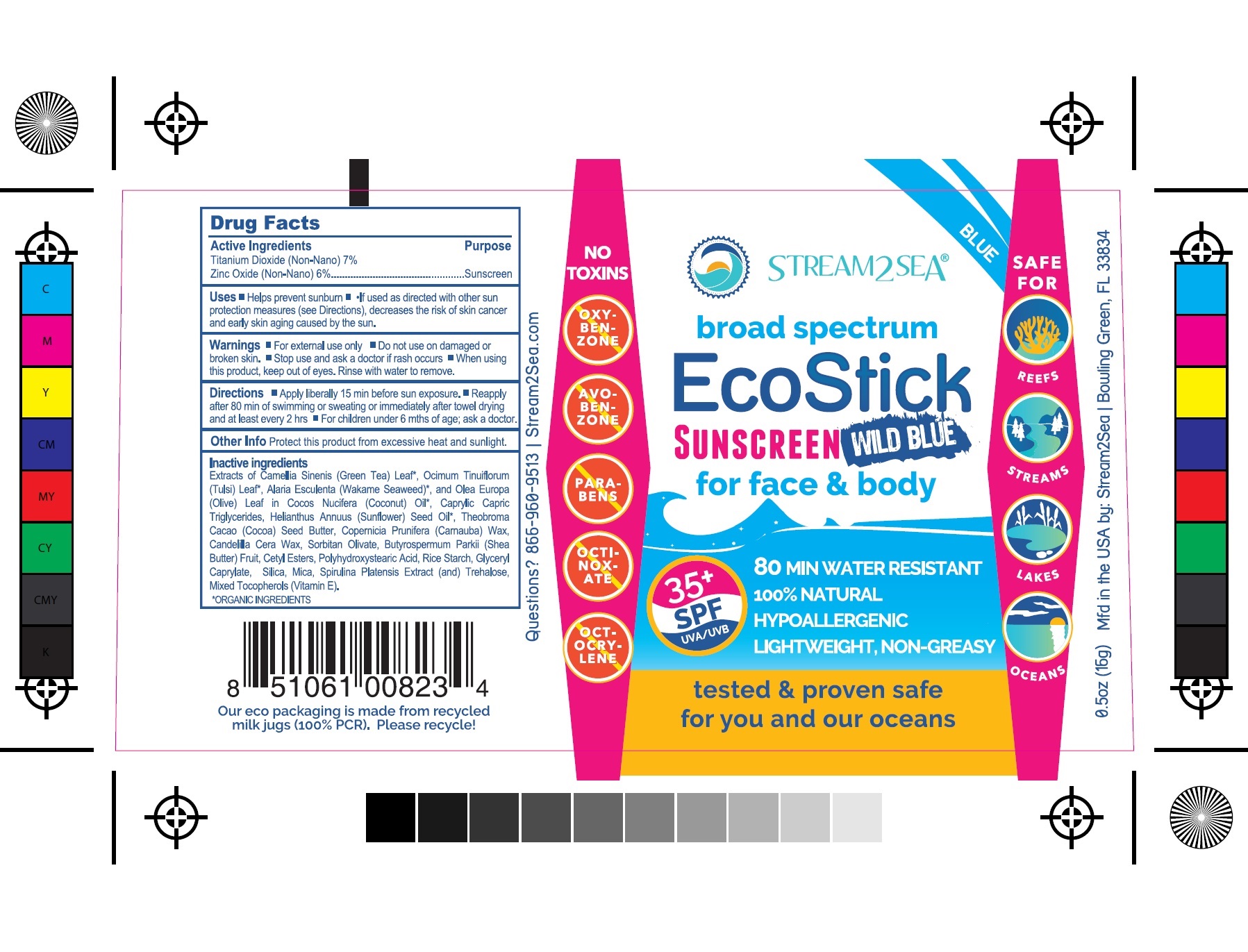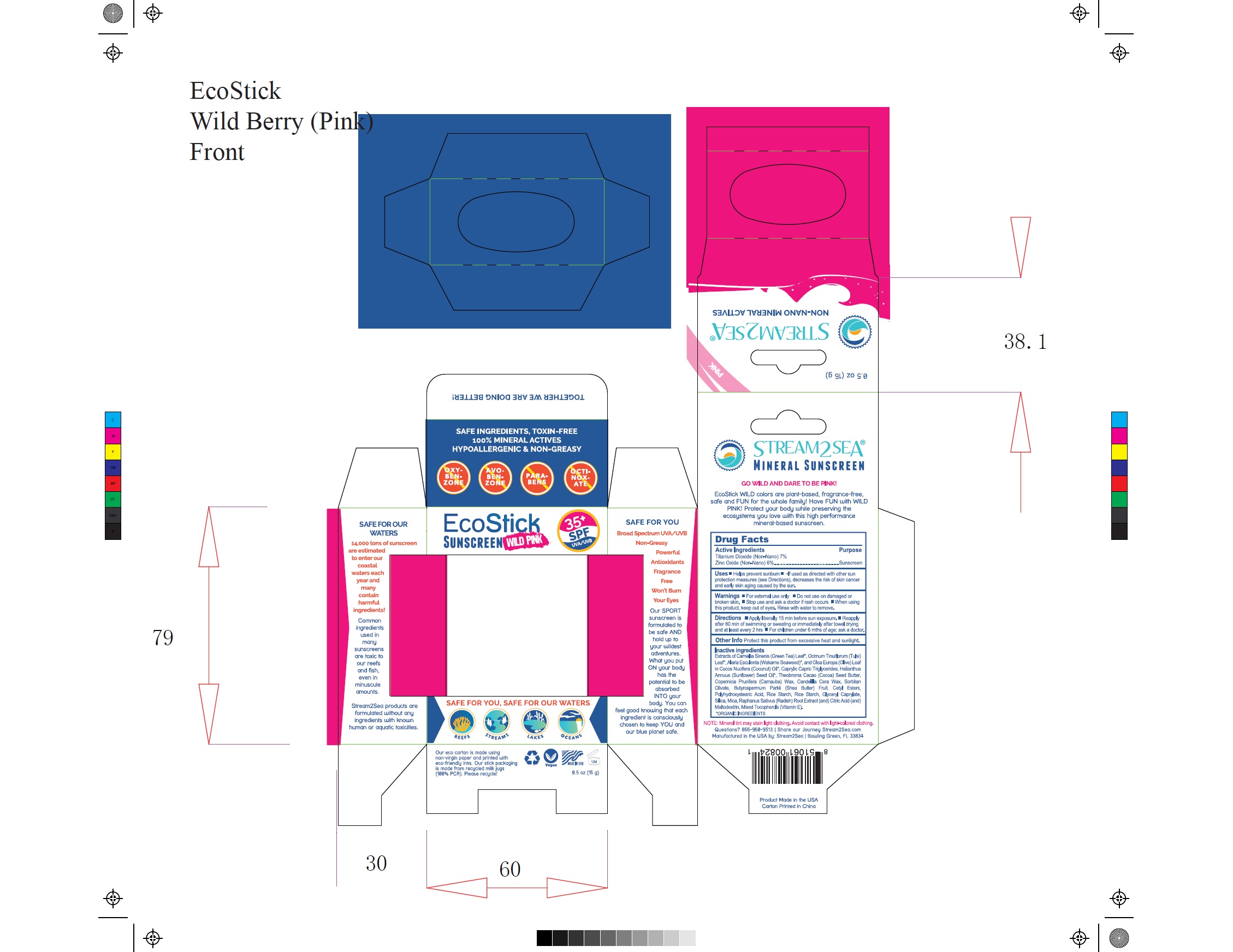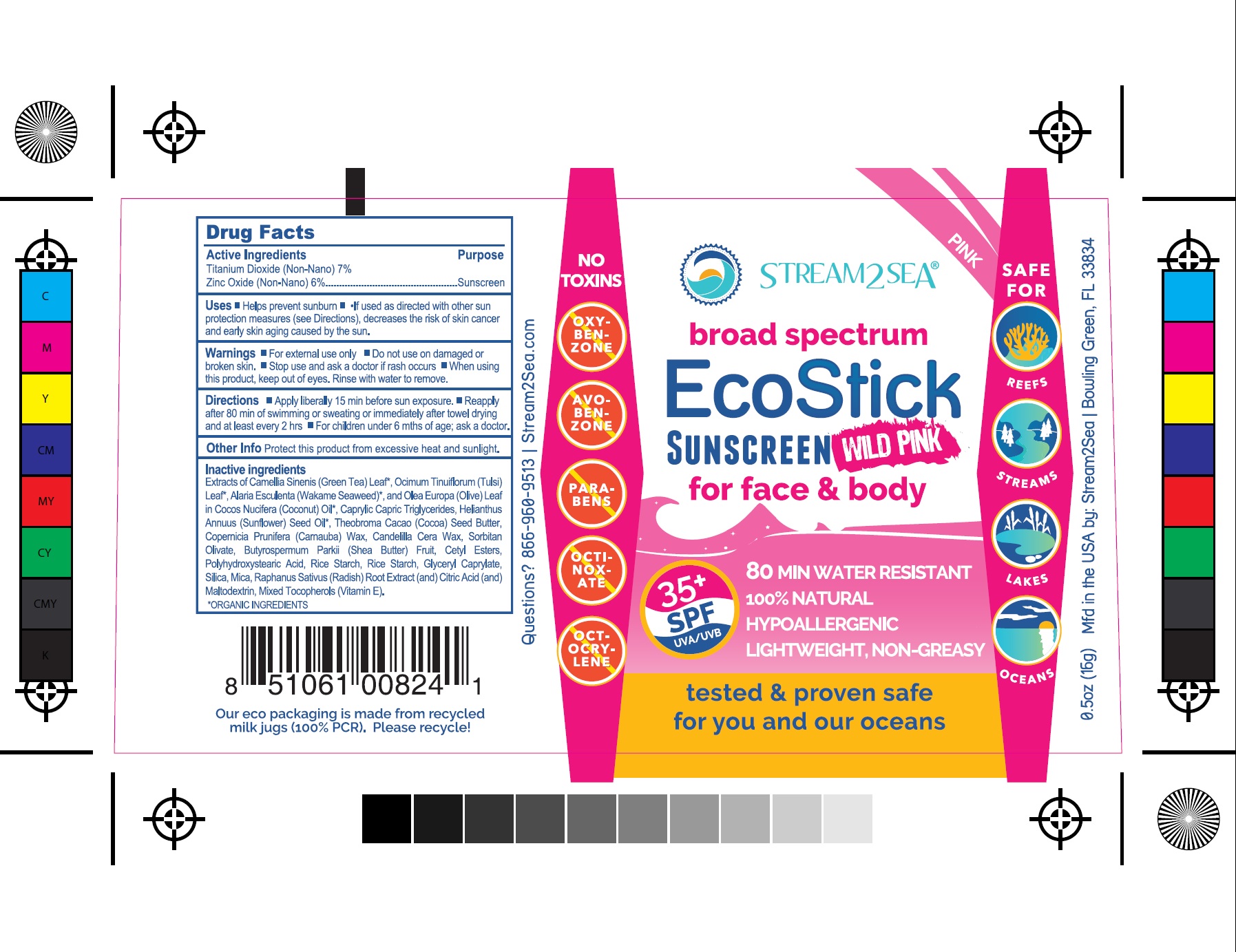 DRUG LABEL: EcoStick Sunscreen
NDC: 69555-035 | Form: STICK
Manufacturer: Stream2Sea, LLC
Category: otc | Type: HUMAN OTC DRUG LABEL
Date: 20241221

ACTIVE INGREDIENTS: ZINC OXIDE 6 g/100 mL; TITANIUM DIOXIDE 7 g/100 mL
INACTIVE INGREDIENTS: GREEN TEA LEAF; HOLY BASIL LEAF; ALARIA ESCULENTA; OLEA EUROPAEA LEAF; COCONUT OIL; MEDIUM-CHAIN TRIGLYCERIDES; SUNFLOWER OIL; COCOA BUTTER; CARNAUBA WAX; CANDELILLA WAX; SORBITAN OLIVATE; BUTYROSPERMUM PARKII (SHEA) BUTTER UNSAPONIFIABLES; CETYL ESTERS WAX; POLYHYDROXYSTEARIC ACID (2300 MW); STARCH, RICE; GLYCERYL MONOCAPRYLATE; SILICON DIOXIDE; MICA; .ALPHA.-TOCOPHEROL; ARTHROSPIRA PLATENSIS; TREHALOSE; RADISH; CITRIC ACID MONOHYDRATE; MALTODEXTRIN; FERRIC OXIDE RED; HYDROLYZED JOJOBA ESTERS (ACID FORM); CHAMOMILE; CALENDULA OFFICINALIS FLOWER

EcoStick Sunscreen SPF 35

Active Ingredients

Titanium Dioxide (Non-Nano) 7%

Zinc Oxide (Non-Nano) 6%

Purpose

Sunscreen

Uses

- Helps prevent sunburn.
- If used as directed with other sun protection measures (see Directions), decreases the risk of skin cancer and early aging caused by the sun.

Warnings

- For external use only
- Do not use on damaged or broken skin
- When using this product keep out of eyes. Rinse with water to remove.
- Stop use and ask a doctor if rash occurs.

- Keep out of reach of children. If product is swallowed, get medical help or contact a Poison Control Center right away.

Directions

- Apply liberally on cleansed skin prior to sun exposure.
- Reapply: after 80 minutes of swimming or sweating / immediately after towel drying / at least every 2 hours
- Sun Protection Measures: Spending time in the sun increases your risk of skin cancer and early skin aging. To decrease this risk, regularly use a sunscreen with a broad spectrum SPF of 15 or higher and other sun protection measures including:
- Limit time in the sun, especially from 10 a.m. - 2 p.m.
- Wear long-sleeved shirts, pants, hats and sunglasses.
- Children under 6 months: Ask a doctor.

Inactive ingredients

Extracts of Camellia Sinenis (Green Tea) Leaf*, Ocimum Tinuiflorum(Tulsi) Leaf*, Alaria Esculenta (Wakame Seaweed)*, and Olea Europa(Olive) Leaf in Cocos Nucifera (Coconut) Oil*, Caprylic CapricTriglycerides, Helianthus Annuus (Sunflower) Seed Oil*,TheobromaCacao (Cocoa) Seed Butter, Copernicia Prunifera (Carnauba) Wax,Candelilla Cera Wax, Sorbitan Olivate, Butyrospermum Parkii (Shea Butter) Fruit, Cetyl Esters, Polyhydroxystearic Acid, Rice Starch, GlycerylCaprylate, Silica, Mica, Mixed Tocopherols (Vitamin E).

WILD BLUE
Extracts of Camellia Sinenis (Green Tea) Leaf*, Ocimum Tinuiflorum (Tulsi) Leaf*, Alaria Esculenta (Wakame Seaweed)*, and Olea Europa(Olive) Leaf in Cocos Nucifera (Coconut) Oil*, Caprylic Capric Triglycerides, Helianthus Annuus (Sunflower) Seed Oil*, Theobroma Cacao (Cocoa) Seed Butter, Copernicia Prunifera (Carnauba) Wax,Candelilla Cera Wax, Sorbitan Olivate, Butyrospermum Parkii (Shea Butter) Fruit, Cetyl Esters, Polyhydroxystearic Acid, Rice Starch, Glyceryl Caprylate, Silica, Mica, Spirulina Platensis Extract (and) Trehalose, Mixed Tocopherols (Vitamin E).

WILD PINK
Extracts of Camellia Sinenis (Green Tea) Leaf*, Ocimum Tinuiflorum (Tulsi) Leaf*, Alaria Esculenta (Wakame Seaweed)*, and Olea Europa (Olive) Leaf in Cocos Nucifera (Coconut) Oil*, Caprylic Capric Triglycerides, Helianthus Annuus (Sunflower) Seed Oil*, Theobroma Cacao (Cocoa) Seed Butter, Copernicia Prunifera (Carnauba) Wax, Candelilla Cera Wax, Sorbitan Olivate, Butyrospermum Parkii (Shea Butter) Fruit, Cetyl Esters, Polyhydroxystearic Acid, Rice Starch, Rice Starch, Glyceryl Caprylate, Silica, Mica, Raphanus Sativus (Radish) Root Extract (and) Citric Acid (and) Maltodextrin, Mixed Tocopherols (Vitamin E).

TINTED
Extracts of Camellia Sinenis (Green Tea) Leaf*, Ocimum Tinuiflorum (Tulsi) Leaf*, Alaria Esculenta (Wakame Seaweed)*, and Olea Europa (Olive) Leaf in Cocos Nucifera (Coconut) Oil*, Caprylic Capric Triglycerides, Helianthus Annuus (Sunflower) Seed Oil*, Theobroma Cacao (Cocoa) Seed Butter, Copernicia Prunifera (Carnauba) Wax, Candelilla Cera Wax, Sorbitan Olivate, Butyrospermum Parkii (Shea Butter) Fruit, Cetyl Esters, Polyhydroxystearic Acid, Rice Starch, Glyceryl Caprylate, Silica, Mica, Mixed Tocopherols (Vitamin E), Iron Oxides (C.I.77492, C.I. 77491, C.I. 77499) and Jojoba Esters

SUNSCREEN 4 KIDS
Extracts of Chamomilla Recutita (Chamomile) Flower* (and) Calendula Officinalis* (and) Camellia Sinensis (Green Tea) Leaf* (and) Ocimum Tenuiflorum (Tulsi) in Cocos Nucifera (Coconut) Oil*, Caprylic Capric Triglycerides, Helianthus Annuus (Sunflower) Seed Oil*, Theobroma Cacao (Cocoa) Seed Butter, Copernicia Prunifera (Carnauba) Wax, Candelilla Cera Wax, Sorbitan Olivate, Butyrospermum Parkii (Shea Butter) Fruit, Cetyl Esters, Polyhydroxystearic Acid, Rice Starch, Glyceryl Caprylate, Silica, Mica, Mixed Tocopherols (Vitamin E).

Other information

Protect this product from excessive heat and direct sun.

Questions or comments?

call 1.863.473.4223 or visit www.stream2sea.com

PRINCIPAL DISPLAY PANEL

EcoStick Sport Sunscreen Carton Label

EcoStick Sport Sunscreen Container Label

EcoStick Sport Screenscreen Wild Blue Carton Label

EcoStick Sport Screenscreen Wild Blue Container Label

EcoStick Sport Screenscreen Tint Carton Label

EcoStick Sport Screenscreen Tint Container Label

EcoStick Sport Screenscreen Wild Pink Carton Label

EcoStick Sport Screenscreen Wild Pink Container Label

EcoStick Sport Screenscreen 4 Kids Carton Label

EcoStick Sport Screenscreen 4 Kids Container Label